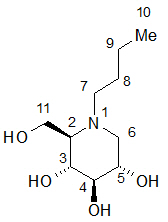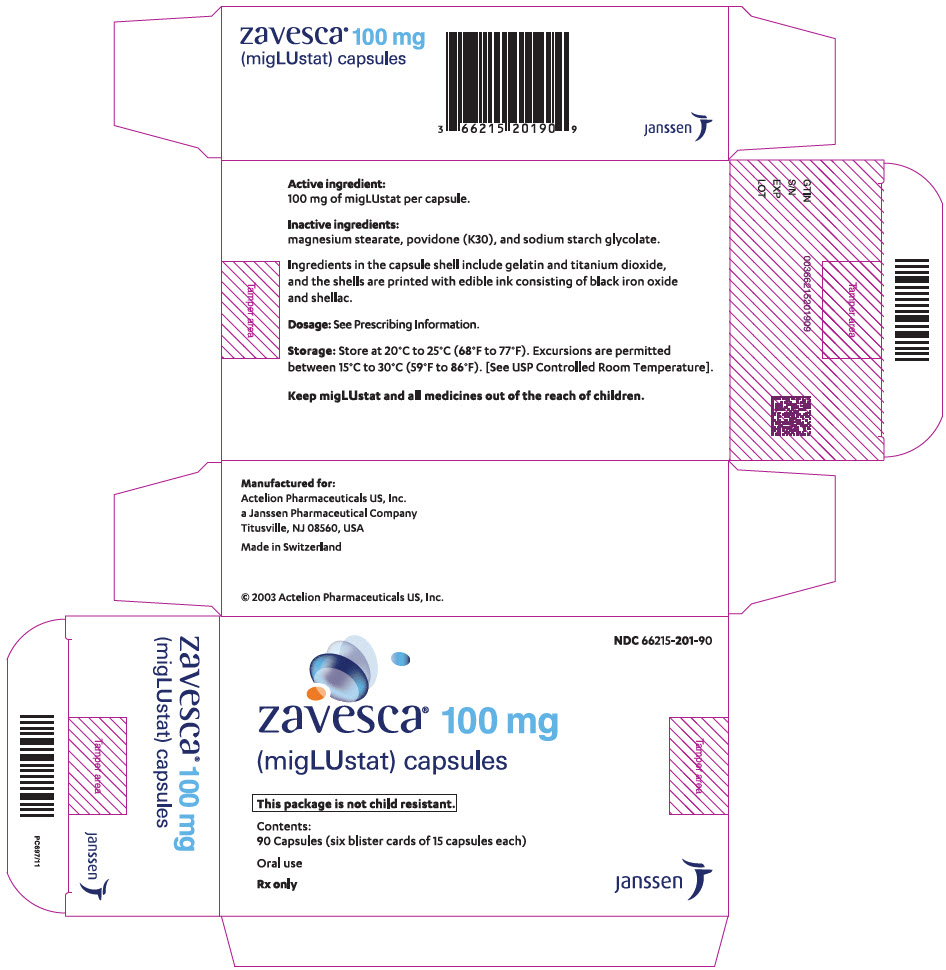 DRUG LABEL: Zavesca
NDC: 66215-201 | Form: CAPSULE
Manufacturer: Actelion Pharmaceuticals US, Inc.
Category: prescription | Type: HUMAN PRESCRIPTION DRUG LABEL
Date: 20230420

ACTIVE INGREDIENTS: MIGLUSTAT 100 mg/1 1
INACTIVE INGREDIENTS: SODIUM STARCH GLYCOLATE TYPE A POTATO; POVIDONE K30; MAGNESIUM STEARATE; GELATIN, UNSPECIFIED; TITANIUM DIOXIDE; FERROSOFERRIC OXIDE; SHELLAC

HIGHLIGHTS OF PRESCRIBING INFORMATION

These highlights do not include all the information needed to use ZAVESCA safely and effectively. See full prescribing information for ZAVESCA.
ZAVESCA® (miglustat) capsules, for oral use
Initial U.S. Approval: 2003

1 INDICATIONS AND USAGE

ZAVESCA is a glucosylceramide synthase inhibitor indicated as monotherapy for treatment of adult patients with mild/moderate type 1 Gaucher disease for whom enzyme replacement therapy is not a therapeutic option (1.1).

2 DOSAGE AND ADMINISTRATION

- Recommended dosage is 100 mg administered orally three times a day at regular intervals (2.1).
- May reduce dosage to 100 mg once or twice a day in some patients due to tremor or diarrhea (2.1).
- Adjust in patients with renal impairment (2.2):

Renal Impairment | Adjusted Creatinine Clearance (in mL/min/1.73 m^2) | Recommendations
Mild | 50 – 70 | Start dose at 100 mg twice a day
Moderate | 30 – 50 | Start dose at 100 mg once a day
Severe | <30 | Use is not recommended

3 DOSAGE FORMS AND STRENGTHS

Capsules: 100 mg (3)

4 CONTRAINDICATIONS

None (4).

5 WARNINGS AND PRECAUTIONS

- Peripheral neuropathy: Perform baseline and follow-up neurological evaluations at 6-month intervals in all patients (5.1).
- Tremor: Reduce dose to ameliorate tremor or discontinue treatment if tremor does not resolve within days of dose reduction (5.2).
- Diarrhea and weight loss: Evaluate for underlying gastrointestinal disease in patients who do not respond to usual interventions (e.g. diet modification) (5.3).
- Reductions in Platelet Count: Mild reductions in platelet counts without association with bleeding were observed in some patients. Monitoring of platelet counts is recommended (5.4).

6 ADVERSE REACTIONS

The most common adverse reactions (incidence ≥5%) are: diarrhea, weight loss, stomach pain, gas, nausea and vomiting headache including migraine, tremor, leg cramps, dizziness, weakness, vision problems, thrombocytopenia, muscle cramps, back pain, constipation, dry mouth, heaviness in arms and legs, memory loss, unsteady walking, anorexia, indigestion, paresthesia, stomach bloating, stomach pain not related to food, and menstrual changes (6.1).

To report SUSPECTED ADVERSE REACTIONS, contact Janssen at 1-800-526-7736 (1-800- JANSSEN) or FDA at 1-800-FDA-1088 or www.fda.gov/medwatch.

7 DRUG INTERACTIONS

Co-administration of ZAVESCA and imiglucerase may lead to increased clearance of imiglucerase (7).

8 USE IN SPECIFIC POPULATIONS

- Pregnancy: Based on animal data, may cause fetal harm (8.1).
- Lactation: Breastfeeding not recommended (8.2).

FULL PRESCRIBING INFORMATION

1 INDICATIONS AND USAGE

1.1 Type 1 Gaucher Disease

ZAVESCA is indicated as monotherapy for the treatment of adult patients with mild to moderate type 1 Gaucher disease for whom enzyme replacement therapy is not a therapeutic option (e.g. due to allergy, hypersensitivity, or poor venous access).

2 DOSAGE AND ADMINISTRATION

2.1 Instructions for Administration

Therapy should be directed by physicians who are knowledgeable in the management of Gaucher disease.

The recommended dose for the treatment of adult patients with type 1 Gaucher disease is one 100 mg capsule administered orally three times a day at regular intervals. If a dose is missed, the next ZAVESCA capsule should be taken at the next scheduled time.

It may be necessary to reduce the dose to one 100 mg capsule once or twice a day in some patients due to adverse reactions, such as tremor or diarrhea.

2.2 Patients with Renal Insufficiency

In patients with mild renal impairment (adjusted creatinine clearance 50–70 mL/min/1.73 m^2), initiate ZAVESCA treatment at a dose of 100 mg twice per day. In patients with moderate renal impairment (adjusted creatinine clearance of 30–50 mL/min/1.73 m^2), initiate ZAVESCA treatment at a dose of one 100 mg capsule per day. ZAVESCA is not recommended for use in patients with severe renal impairment (creatinine clearance <30 mL/min/1.73 m^2) [see Use in Specific Populations (8.6)].

3 DOSAGE FORMS AND STRENGTHS

Capsules: 100 mg of miglustat, white opaque hard gelatin capsules with "OGT 918" printed in black on the cap and "100" printed in black on the body.

4 CONTRAINDICATIONS

None.

5 WARNINGS AND PRECAUTIONS

5.1 Peripheral Neuropathy

In clinical trials, cases of peripheral neuropathy have been reported in 3% of Gaucher's patients treated with ZAVESCA. All patients receiving ZAVESCA treatment should undergo baseline and repeat neurological evaluations at approximately 6-month intervals. Patients who develop symptoms of peripheral neuropathy such as pain, weakness, numbness and tingling should have a careful re-assessment of the risk/benefit of ZAVESCA therapy, and cessation of treatment may be considered.

5.2 Tremor

Approximately 30% of patients have reported tremor or exacerbation of existing tremor on treatment. These tremors were described as an exaggerated physiological tremor of the hands. Tremor usually began within the first month of therapy and in many cases resolved between 1 to 3 months during treatment. Reduce dose to ameliorate tremor or discontinue treatment if tremor does not resolve within days of dose reduction.

5.3 Diarrhea and Weight Loss

Diarrhea and weight loss were common in clinical studies of patients treated with ZAVESCA, occurring in approximately 85% and up to 65% of treated patients, respectively. Diarrhea appears to be the result of the inhibitory activity of ZAVESCA on intestinal disaccharidases such as sucrase-isomaltase in the gastrointestinal tract leading to reduced absorption of dietary disaccharides in the small intestine, with a resultant osmotic diarrhea. It is unclear if weight loss results from the diarrhea and associated gastrointestinal complaints, a decrease in food intake, or a combination of these or other factors. The incidence of weight loss was most evident in the first 12 months of treatment. Diarrhea decreased over time with continued ZAVESCA treatment, and may respond to individualized diet modification (e.g., reduction of sucrose, lactose and other carbohydrate intake), to taking ZAVESCA between meals, and/or to anti-diarrheal medications, most commonly loperamide. Patients may be instructed to avoid high carbohydrate content foods during treatment with ZAVESCA if they present with diarrhea.

Patients with persistent gastrointestinal events that continue during treatment with ZAVESCA, and who do not respond to usual interventions (e.g. diet modification), should be evaluated to determine whether significant underlying gastrointestinal disease is present. The safety of treatment with ZAVESCA has not been evaluated in patients with significant gastrointestinal disease, such as inflammatory bowel disease, and continued treatment of these patients with ZAVESCA should occur only after consideration of the risks and benefits of continued treatment.

5.4 Reductions in Platelet Count

In clinical trials evaluating the use of ZAVESCA for treatment of indications other than type 1 Gaucher disease, mild reductions in platelet counts without association with bleeding were observed in some patients; approximately 40% of patients in this trial had low platelet counts (defined as below 150×10^9/L) before starting treatment with ZAVESCA. Monitoring of platelet counts is recommended in patients with type 1 Gaucher disease. Mild reductions in platelet counts without association with bleeding were observed in patients with type 1 Gaucher disease who were switched from enzyme replacement therapy (ERT) to ZAVESCA.

6 ADVERSE REACTIONS

The following serious adverse reactions are described below and elsewhere in the labeling:

- Peripheral Neuropathy [see Warnings and Precautions (5.1)]
- Tremor [see Warnings and Precautions (5.2)]
- Diarrhea and Weight Loss [see Warnings and Precautions (5.3)]
- Reductions in Platelet Count [see Warnings and Precautions (5.4)]

6.1 Clinical Trials Experience

Because clinical trials are conducted under widely varying conditions, adverse reaction rates observed in the clinical trials of a drug cannot be directly compared to rates in the clinical trials of another drug and may not reflect the rates observed in practice.

The data described below reflect exposure of 80 patients with type 1 Gaucher disease in two open-label, uncontrolled, monotherapy trials, one open-label, active-controlled trial, and two extensions, who received ZAVESCA at doses ranging from 50 mg to 200 mg three times daily. Patients were aged 18 to 69 years at first treatment. The population was evenly distributed by gender.

The most common serious adverse reaction reported with ZAVESCA treatment in clinical trials was peripheral neuropathy [see Warnings and Precautions (5.1)].

The most commonly reported adverse reactions in patients treated with ZAVESCA (occurring in ≥5%) that were considered related to ZAVESCA are shown in Tables 1 and 2 [see Warnings and Precautions (5.2, 5.3)].

The most common adverse reactions requiring intervention were diarrhea and tremor [see Warnings and Precautions (5.2, 5.3)].

In two open-label, uncontrolled monotherapy trials, adult type 1 Gaucher disease patients were treated with ZAVESCA at a starting dose of 100 mg three times daily (dose range 100 to 200 mg three times daily) for up to 12 months in 28 patients [Study 1], or at a dose of 50 mg three times daily for up to 6 months in 18 patients [Study 2]. Table 1 below lists adverse reactions that occurred during the trials in ≥5% of patients.

Table 1: Adverse Reactions in ≥5% of Patients in Two Open-Label, Uncontrolled Monotherapy Trials of ZAVESCA
 | Incidence of adverse reactions
 | Study 1 (starting dose 100 mg three times daily) | Study 2 (50 mg three times daily)
Patients entered in Study (n) | 28 | 18
Body System - Preferred Term | % of patients reporting | % of patients reporting
Gastrointestinal System
Diarrhea | 89 | 89
Flatulence | 29 | 44
Abdominal Pain | 18 | 50
Nausea | 14 | 22
Vomiting | 4 | 11
Bloating | 0 | 6
Anorexia | 7 | 0
Dyspepsia | 7 | 0
Epigastric pain not food-related | 0 | 6
Metabolic and Nutritional Disorders
Weight Decrease | 39 | 67
Central and Peripheral Nervous System
Headache | 21 | 22
Tremor | 11 | 11
Dizziness | 0 | 11
Leg cramps | 4 | 11
Paresthesia | 7 | 0
Migraine | 0 | 6
Vision Disorders
Visual Disturbance | 0 | 17
Musculoskeletal Disorders
Cramps | 0 | 11
Platelet, Bleeding, and Clotting Disorders
Thrombocytopenia | 7 | 6
Reproductive disorders, female
Menstrual disorder | 0 | 6

In an open-label, active-controlled study, 36 adult type 1 Gaucher disease patients were treated with ZAVESCA, imiglucerase, or ZAVESCA plus imiglucerase [Study 3] for up to 12 months. Table 2 lists adverse reactions that occurred during the trial in ≥5% of patients.

Table 2: Adverse Reactions in ≥5% of Patients in Open-Label Active Controlled Study
 | Incidence of adverse reactions
 | ZAVESCA alone | Imiglucerase alone
Patients entered in Study (n) | 12 | 12
Body System - Preferred Term | % of patients reporting | % of patients reporting
Gastrointestinal System
Diarrhea | 100 | 0
Abdominal Pain | 67 | 0
Flatulence | 50 | 0
Constipation | 8 | 0
Nausea | 8 | 0
Dry Mouth | 8 | 0
Body as a Whole
Pain | 0 | 8
Generalized weakness | 17 | 0
Abdominal distension | 8 | 0
Back pain | 8 | 0
Heaviness in limbs | 8 | 0
Metabolic and Nutritional Disorders
Weight Decrease | 67 | 0
Central and Peripheral Nervous System
Tremor | 17 | 0
Dizziness | 8 | 0
Leg cramps | 8 | 0
Unsteady gait | 8 | 0
Psychiatric disorders
Memory loss | 8 | 0

7 DRUG INTERACTIONS

While co-administration of ZAVESCA appeared to increase the clearance of imiglucerase by 70%, these results are not conclusive because of the small number of patients studied and because patients took variable doses of imiglucerase [see Clinical Pharmacology (12.3)].

8 USE IN SPECIFIC POPULATIONS

8.1 Pregnancy

Risk Summary

Based on findings from animal reproduction studies, ZAVESCA may cause fetal harm when administered to a pregnant woman. Available data from postmarketing case reports with ZAVESCA use in pregnancy are insufficient to assess a drug-associated risk of major birth defects, miscarriage, or adverse maternal or fetal outcomes. There are risks associated with symptomatic Type I Gaucher disease in pregnancy, including hepatosplenomegaly and thrombocytopenia (see Clinical Considerations). Advise pregnant women of the potential risks to the fetus.

In animal reproduction studies, miglustat was maternally toxic in rabbits at exposures near the expected human therapeutic dose and caused embryo-fetal toxicities in rats at doses twice the recommended human dose. No adverse developmental outcomes were observed with administration of miglustat to pregnant rats at dose levels 6 times the recommended human dose. (see Data).

The estimated background risk of major birth defects and miscarriage for the indicated population is unknown. All pregnancies have a background risk of birth defect, loss, or other adverse outcomes. In the U.S. general population, the estimated background risk of major birth defects and miscarriage in clinically recognized pregnancies is 2–4% and 15–20%, respectively.

Clinical Considerations

Disease-associated Maternal and Embryo-Fetal Risk

Pregnancy may exacerbate existing Type 1 Gaucher disease symptoms or result in new disease manifestations. Type 1 Gaucher disease manifestations may lead to adverse pregnancy outcomes including, hepatosplenomegaly which can interfere with the normal growth of a pregnancy and thrombocytopenia which can lead to increased bleeding and possible hemorrhage.

Data

Animal Data

In female rats given miglustat by oral gavage at doses of 20, 60, 180 mg/kg/day beginning 14 days before mating and continuing through gestation day 17 (organogenesis), increased post implantation loss, decreased embryo-fetal survival and decreased fetal and pup weights were observed at doses ≥60 mg/kg/day (≥2 times the human therapeutic dose on a mg/m^2 basis). Miglustat was also administered to pregnant rats by oral gavage at doses of 20, 60, 180 mg/kg/day from gestation day 6 through lactation (postpartum day 20). Delayed and prolonged parturition with decreased live births were observed at doses ≥60 mg/kg/day (≥2 times the human therapeutic dose on a mg/m^2 basis).

In pregnant rabbits given miglustat by oral gavage at doses of 15, 30, 45 mg/kg/day during gestation days 6–18 (organogenesis), maternal toxicity, including maternal deaths (all doses), reduced food consumption (30 and 45 mg/kg/day), and decreased body weight gain (15 and 30 mg/kg/day), was observed. The 15 mg/kg/day dose level was 0.97 times the human therapeutic dose on a mg/m^2 basis.

In a pre- and postnatal development study in rats, miglustat was administered by oral gavage at doses of 20, 60, 180 mg/kg/day from gestation day 6 through day 20 of lactation, decreased live births were observed in dams, as well as decreased body weight gain in the offspring at doses ≥60 mg/kg/day (≥2 times the human therapeutic dose on a mg/m^2 basis). There was no effect on behavioral and learning assessments, sexual maturation or reproductive performance of the offspring at doses up to 180 mg/kg/day (about 6 times the human therapeutic dose on a mg/m^2 basis).

8.2 Lactation

Risk Summary

There are no available data on the presence of miglustat in either human or animal milk, the effects on the breastfed infant, or the effects on milk production. Based on the physical properties of miglustat, ZAVESCA is likely to be present in breast milk. Because of the potential for serious adverse reactions in breastfed infants, advise women that breastfeeding is not recommended.

8.3 Females and Males of Reproductive Potential

Infertility

Findings from a small clinical study in seven healthy adult males who received miglustat for six weeks did not indicate effects on male fertility. Studies in male rats have shown that miglustat decreased fertility but findings were reversible. Studies in female rats have shown increased post-implantation loss and decreased embryo-fetal survival [see Use in Specific Populations (8.1), Nonclinical Toxicology (13.1)] .

8.4 Pediatric Use

The safety and effectiveness of ZAVESCA in pediatric patients have not been established.

In a combined clinical trial safety data set of 45 patients less than 18 years of age exposed to ZAVESCA in indications other than type 1 Gaucher disease, the median weight and height percentiles adjusted for age and gender decreased during the first year of treatment but then stabilized. The mean length of exposure in these studies ranged from 2 to 2.6 years; some pediatric patients were exposed for up to 4 years. However, the effect of ZAVESCA on long-term gain in weight and height in pediatric patients is unclear.

8.5 Geriatric Use

Clinical studies of ZAVESCA did not include sufficient numbers of patients aged 65 and over to determine whether they respond differently than younger patients. Other reported clinical experience has not identified differences in responses between elderly and younger patients. In general, dose selection for an elderly patient should be cautious, usually starting at the low end of the dosing range, reflecting the greater frequency of decreased hepatic, renal, and cardiac function and of concomitant disease or other drug therapy.

8.6 Renal Impairment

Miglustat is known to be substantially excreted by the kidney, and the risk of adverse reactions to this drug may be greater in patients with impaired renal function [see Clinical Pharmacology (12.3)].

In patients with mild renal impairment (adjusted creatinine clearance 50–70 mL/min/1.73 m^2), ZAVESCA administration should commence at a dose of 100 mg twice per day.

In patients with moderate renal impairment (adjusted creatinine clearance of 30–50 mL/min/1.73 m^2), ZAVESCA administration should commence at a dose of 100 mg once a day.

Use of ZAVESCA in patients with severe renal impairment (creatinine clearance <30 mL/min/1.73 m^2) is not recommended .

Since elderly patients are more likely to have decreased renal function, care should be taken in dose selection, and it may be useful to monitor renal function . The impact of hemodialysis on the disposition of ZAVESCA has not been investigated.

11 DESCRIPTION

ZAVESCA® (miglustat capsules, 100 mg) is a glucosylceramide synthase inhibitor, which is a glucosyl transferase enzyme responsible for the first step in the synthesis of most glycosphingolipids. ZAVESCA is an N-alkylated imino sugar, a synthetic analog of D-glucose.

The chemical name for miglustat is 1,5-(butylimino)-1,5-dideoxy-D-glucitol with the chemical formula C10H21NO4 and a molecular weight of 219.28.

Miglustat is a white to off-white crystalline solid and has a bitter taste. It is highly soluble in water (>1000 mg/mL as a free base).

ZAVESCA is supplied in hard gelatin capsules each containing 100 mg miglustat for oral administration. Each ZAVESCA 100 mg capsule also contains magnesium stearate, povidone (K30), and sodium starch glycolate. Ingredients in the capsule shell include gelatin and titanium dioxide, and the shells are printed with edible ink consisting of black iron oxide and shellac.

12 CLINICAL PHARMACOLOGY

12.1 Mechanism of Action

Type 1 Gaucher disease is caused by a functional deficiency of glucocerebrosidase, the enzyme that mediates the degradation of the glycosphingolipid glucosylceramide.

Miglustat functions as a competitive and reversible inhibitor of the enzyme glucosylceramide synthase, the initial enzyme in a series of reactions which results in the synthesis of most glycosphingolipids.

ZAVESCA helps reduce the rate of glycosphingolipid biosynthesis so that the amount of glycosphingolipid substrate is reduced to a level which allows the residual activity of the deficient glucocerebrosidase enzyme to be more effective (substrate reduction therapy). In vitro and in vivo studies have shown that miglustat can reduce the synthesis of glucosylceramide-based glycosphingolipids.

12.3 Pharmacokinetics

Absorption

After a 100 mg oral dose, the time to maximum observed plasma concentration of miglustat (tmax) ranged from 2 to 2.5 hours in Gaucher patients. Plasma concentrations show a biexponential decline, characterized by a short distribution phase and a longer elimination phase. The effective half-life of miglustat is approximately 6 to 7 hours, which predicts that steady-state will be achieved by 1.5 to 2 days following the start of three times daily dosing.

Miglustat, dosed at 50 and 100 mg three times daily in Gaucher patients, exhibits dose-proportional pharmacokinetics. The pharmacokinetics of miglustat were not altered after repeated dosing three times daily for up to 12 months.

In healthy subjects, co-administration of ZAVESCA with food results in a decrease in the rate of absorption of miglustat (maximum plasma concentration [Cmax] was decreased by 36% and tmax delayed 2 h) but had no statistically significant effect on the extent of absorption of miglustat (area-under-the-plasma-concentration time curve [AUC] was decreased by 14%). The mean oral bioavailability of a 100-mg miglustat capsule is about 97% relative to an oral solution administered under fasting conditions. The pharmacokinetics of miglustat were similar between adult type 1 Gaucher disease patients and healthy subjects after a single dose administration of miglustat 100 mg.

Distribution

Miglustat does not bind to plasma proteins. Mean apparent volume of distribution of miglustat is 83–105 liters in Gaucher patients. At steady state, the concentration of miglustat in cerebrospinal fluid of six non-Gaucher patients was 31.4–67.2% of that in plasma, indicating that miglustat crosses the blood brain barrier.

Metabolism and Excretion

The major route of excretion of miglustat is via kidney. Following administration of a single dose of 100 mg^14C-miglustat to healthy volunteers, 83% of the radioactivity was recovered in urine and 12% in feces. In healthy subjects, 67% of the administered dose was excreted unchanged in urine over 72 hours. The most abundant metabolite in urine was miglustat glucuronide accounting for 5% of the dose. The terminal half-life of radioactivity in plasma was 150 hours, suggesting the presence of one or more metabolites with a prolonged half-life. The metabolite accounting for this observation has not been identified, but may accumulate and reach concentrations exceeding those of miglustat at steady state.

Specific Populations

Gender

There was no statistically significant gender difference in miglustat pharmacokinetics, based on pooled data analysis.

Race

Ethnic differences in miglustat pharmacokinetics have not been evaluated in Gaucher patients. However, apparent oral clearance of miglustat in patients of Ashkenazi Jewish descent was not statistically different to that in others (1 Asian and 15 Caucasians), based on a cross-study analysis.

Hepatic Impairment

No studies have been performed to assess the pharmacokinetics of miglustat in patients with hepatic impairment.

Renal Impairment

Limited data in non-Gaucher patients with impaired renal function indicate that the apparent oral clearance (CL/F) of miglustat decreases with decreasing renal function. While the number of subjects with mild and moderate renal impairment was very small, the data suggest an approximate decrease in the apparent oral clearance of 40% and 60% respectively, in mild and moderate renal impairment, justifying the need to decrease the dosing of miglustat in such patients dependent upon creatinine clearance levels [see Dosage and Administration (2.2)].

Data in severe renal impairment are limited to two patients with creatinine clearances in the range 18–29 mL/min and cannot be extrapolated below this range. These data suggest a decrease in CL/F by at least 70% in patients with severe renal impairment [see Dosage and Administration (2.2) and Use in Specific Populations (8.6)].

Drug Interaction Studies

Miglustat does not inhibit the metabolism of various substrates of cytochrome P450 enzymes including, CYP1A2, CYP2A6, CYP2C9, CYP2C19, CYP2D6, CYP2E1, CYP3A4 and CYP4A11 in vitro; consequently, significant interactions via inhibition of these enzymes are unlikely with drugs that are substrates of cytochrome P450 enzymes.

Drug interaction between ZAVESCA (miglustat 100 mg orally three times daily) and imiglucerase 7.5 or 15 U/kg/day was assessed in imiglucerase-stabilized patients after one month of co-administration. There was no significant effect of imiglucerase on the pharmacokinetics of miglustat, with the co-administration of imiglucerase and miglustat resulting in a 22% reduction in Cmax and a 14% reduction in the AUC for miglustat. While ZAVESCA appeared to increase the clearance of imiglucerase by 70%, these results are not conclusive because of the small number of subjects studied and because patients took variable doses of imiglucerase [see Drug Interactions (7)].

Concomitant therapy with loperamide during clinical trials did not appear to significantly alter the pharmacokinetics of miglustat.

13 NONCLINICAL TOXICOLOGY

13.1 Carcinogenesis, Mutagenesis, Impairment of Fertility

Carcinogenesis

Two-year carcinogenicity studies have been conducted with miglustat in CD-1 mice at oral doses up to 500 mg/kg/day and in Sprague Dawley rats at oral doses up to 180 mg/kg/day. Oral administration of miglustat for 104 weeks produced mucinous adenocarcinomas of the large intestine at 210, 420 and 500 mg/kg/day (about 3, 6 and 7 times the recommended human dose, respectively, based on the body surface area) in male mice and at 420 and 500 mg/kg/day (about 6 and 7 times the recommended human dose, based on the body surface area) in female mice. The adenocarcinomas were considered rare in CD-1 mice and occurred in the presence of inflammatory and hyperplastic lesions in the large intestine of both males and females. In rats, oral administration of miglustat for 100 weeks produced increased incidences of interstitial cell adenomas of the testis at 30, 60 and 180 mg/kg/day (about 1, 2 and 5 times the recommended human dose, respectively, based on the body surface area).

Mutagenesis

Miglustat was not mutagenic or clastogenic in a battery of in vitro and in vivo assays including the bacterial reverse mutation (Ames), chromosomal aberration (in human lymphocytes), gene mutation in mammalian cells (Chinese hamster ovary), and mouse micronucleus assays.

Impairment of Fertility

Miglustat was administered by oral gavage to male rats at doses of 20, 60, 180 mg/kg/day beginning at least 14 days prior to mating and continuing through mating. Effects on sperm parameters (concentration, motility and morphology) resulting in decreased fertility were observed at all dose levels (the lowest dose level was 0.65 times the human therapeutic dose on a mg/m^2 basis). Reversibility was demonstrated following 6 weeks of drug withdrawal. Findings of, seminiferous tubule degeneration and atrophy were observed in the testes in rat repeat-dose toxicity studies.

Miglustat was administered by oral gavage to female rats at doses of 20, 60, 180 mg/kg/day beginning 14 days before mating and continuing through gestation day 17. There were no effects on mating performance or fertility in female rats at doses up to 180 mg/kg/day. However, increased post implantation loss and decreased embryo-fetal survival were observed at doses ≥60 mg/kg/day (≥2 times the human therapeutic dose on a mg/m^2 basis).

13.2 Animal Toxicology and/or Pharmacology

Histopathology findings in the absence of clinical signs in the central nervous system of the monkey (brain, spine) that included vascular mineralization, in addition to mineralization and necrosis of white matter were observed at >750 mg/kg/day (4 times the human therapeutic systemic exposure based on area-under-the-plasma-concentration curve [AUC] comparisons) in a 52-week oral toxicity study using doses of 750 and 2000 mg/kg/d. Vacuolization of white matter was observed in rats dosed orally by gavage at ≥180 mg/kg/d (6 times the human therapeutic exposure based on surface area comparisons, mg/m^2) in a 4-week study using doses of 180, 840, and 4200 mg/kg/d. Vacuolization can sometimes occur as an artifact of tissue processing. Findings in dogs included tremor and absent corneal reflexes at 105 mg/kg/day (10 times the human therapeutic systemic exposure, based on body surface area comparisons, mg/m^2) after a 4-week oral gavage toxicity study using doses of 35, 70, 105, and 140 mg/kg/d. Ataxia, diminished/absent pupillary, palpebral, or patellar reflexes were observed in a dog at ≥495 mg/kg/day (50 times the human therapeutic systemic exposure based on body surface area comparisons, mg/m^2), in a 2-week oral gavage toxicity study using doses of 85, 165, 495, and 825 mg/kg/d.

Cataracts were observed in rats at ≥180 mg/kg/day (4 times the human therapeutic systemic exposure, based on AUC) in a 52-week oral gavage toxicity study using doses of 180, 420, 840, and 1680 mg/kg/d.

Gastrointestinal necrosis, inflammation, and hemorrhage were observed in dogs at ≥85 mg/kg/day (9 times the human therapeutic systemic exposure based on body surface area comparisons, mg/m^2) after a 2-week oral (capsule) toxicity study using doses of 85, 165, 495, and 825 mg/kg/d. Similar GI toxicity occurred in rats at 1200 mg/kg/day (7 times the human therapeutic systemic exposure, based on AUC) in a 26-week oral gavage toxicity study using doses of 300, 600, and 1200 mg/kg/d. In monkeys, similar GI toxicity occurred at ≥750 mg/kg/day (6 times the human therapeutic systemic exposure based on AUC) following a 52-week oral gavage toxicity study using doses of 750 and 2000 mg/kg/d.

14 CLINICAL STUDIES

The efficacy of ZAVESCA in type 1 Gaucher disease has been investigated in two open-label, uncontrolled trials and one randomized, open-label, active-controlled trial with enzyme replacement given as imiglucerase. Patients who received ZAVESCA were treated with doses ranging from 100 to 600 mg a day, although the majority of patients were maintained on doses between 200 to 300 mg a day. Efficacy parameters included the evaluation of liver and spleen organ volume, hemoglobin concentration, and platelet count. A total of 80 patients were exposed to ZAVESCA during the three trials and their extension period.

Open-Label Uncontrolled Monotherapy Trials

In Study 1, ZAVESCA was administered at a starting dose of 100 mg three times daily for 12 months (dose range of 100 once-daily to 200 mg three times daily) to 28 adult patients with type 1 Gaucher disease, who were unable to receive enzyme replacement therapy and who had not taken enzyme replacement therapy in the preceding 6 months. Twenty-two patients completed the trial. After 12 months of treatment, the results showed significant mean percent reductions from baseline in liver volume of 12% and spleen volume of 19%, a non-significant increase from baseline in mean absolute hemoglobin concentration of 0.26 g/dL and a mean absolute increase from baseline in platelet counts of 8×10^9/L (See Tables 3–6).

In Study 2, ZAVESCA was administered at a dose of 50 mg three times daily for 6 months to 18 adult patients with type 1 Gaucher disease who were unable to receive enzyme replacement therapy and who had not taken enzyme replacement therapy in the preceding 6 months. Seventeen patients completed the trial. After 6 months of treatment, the results showed significant mean percent reductions from baseline in liver volume of 6% and spleen volume of 5%. There was a non-significant mean absolute decrease from baseline in hemoglobin concentration of 0.13 g/dL and a non-significant mean absolute increase from baseline in platelet counts of 5×10^9/L (See Tables 3–6).

Extension Period

Eighteen patients were enrolled in a 12-month extension to Study 1. A subset of patients continuing in the extension had larger mean baseline liver volumes, and lower mean baseline platelet counts and hemoglobin concentrations than the original study population (See Tables 3–6). After a total of 24 months of treatment, there were significant mean decreases from baseline in liver and spleen organ volumes of 15% and 27%, respectively, and significant mean absolute increases from baseline in hemoglobin concentration and platelet count of 0.9 g/dL and 14×10^9/L, respectively (See Tables 3–6).

Sixteen patients were enrolled in a 6-month extension to Study 2. After a total of 12 months of treatment, there was a mean decrease from baseline in spleen organ volume of 10%, whereas the mean percent decrease in liver organ volume remained at 6%. There were no significant changes in hemoglobin concentrations or platelet counts (See Tables 3–6).

Liver volume results from Studies 1 and 2 and their extensions are summarized in Table 3:

Table 3: Liver Volume Changes in Two Open-Label Uncontrolled Monotherapy Trials of ZAVESCA with Extension Period
 |  | Liver Volume
 | n | Absolute Mean (L) (2-sided 95% CI) | Percent Mean (%) (2-sided 95% CI)
Study 1 (starting dose ZAVESCA 100 mg three times daily)
Baseline (Month 0) | 21 | 2.39
Month 12 Change from baseline |  | -0.28 (-0.38, -0.18) | -12.1% (-16.4, 7.9)
Study 1 Extension Phase
Baseline (Month 0) | 12 | 2.54
Month 24 Change from baseline |  | -0.36 (-0.48, -0.24) | -14.5% (-19.3, 9.7)
Study 2 (ZAVESCA 50 mg three times daily)
Baseline (Month 0) | 17 | 2.45
Month 6 Change from baseline |  | -0.14 (-0.25, -0.03) | -5.9% (-9.9, -1.9)
Study 2 Extension Phase
Baseline (Month 0) | 13 | 2.35
Month 12 Change from baseline |  | -0.17 (-0.3, -0.0) | -6.2% (-12.0, -0.5)

Spleen volume results from Studies 1 and 2 and their extensions are summarized in Table 4:

Table 4: Spleen Volume Changes in Two Open-Label Uncontrolled Monotherapy Trials of ZAVESCA with Extension Period
 |  | Spleen Volume
 | n | Absolute Mean (L) (2-sided 95% CI) | Percent Mean (%) (2-sided 95% CI)
Study 1 (starting dose ZAVESCA 100 mg three times daily)
Baseline (Month 0) | 18 | 1.64
Month 12 Change from baseline |  | -0.32 (-0.42, -0.22) | -19.0% (-23.7, -14.3)
Study 1 Extension Phase
Baseline (Month 0) | 10 | 1.56
Month 24 Change from baseline |  | -0.42 (-0.53, -0.30) | -26.4% (-30.4, -22.4)
Study 2 (ZAVESCA 50 mg three times daily)
Baseline (Month 0) | 11 | 1.98
Month 6 Change from baseline |  | -0.09 (-0.18, -0.01) | -4.5% (-8.2, -0.7)
Study 2 Extension Phase
Baseline (Month 0) | 9 | 1.98
Month 12 Change from baseline |  | -0.23 (-0.46, 0.00) | -10.1% (-20.1, -0.1)

Hemoglobin concentration results from Studies 1 and 2 and their extensions are summarized in Table 5:

Table 5: Hemoglobin Concentration Changes in Two Open-Label Uncontrolled Monotherapy Trials of ZAVESCA with Extension Period
 |  | Hemoglobin Concentration
 | n | Absolute Mean (g/dL) (2-sided 95% CI) | Percent Mean (%) (2-sided 95% CI)
Study 1 (starting dose ZAVESCA 100 mg three times daily)
Baseline (Month 0) | 22 | 11.94
Month 12 Change from baseline |  | 0.26 (-0.05, 0.57) | 2.6% (-0.5, 5.7)
Study 1 Extension Phase
Baseline (Month 0) | 13 | 11.03
Month 24 Change from baseline |  | 0.91 (0.30, 1.53) | 9.1% (2.9, 15.2)
Study 2 (ZAVESCA 50 mg three times daily)
Baseline (Month 0) | 17 | 11.60
Month 6 Change from baseline |  | -0.13 (-0.51, 0.24) | -1.3% (-4.4, 1.8)
Study 2 Extension Phase
Baseline (Month 0) | 13 | 11.94
Month 12 Change from baseline |  | 0.06 (-0.73, 0.85) | 1.2% (-5.2, 7.7)

Platelet count results from Studies 1 and 2 and their extensions are summarized in Table 6:

Table 6: Platelet Count Changes in Two Open-Label Uncontrolled Monotherapy Trials of ZAVESCA with Extension Period
 |  | Platelet Count
 | n | Absolute Mean (10^9/L) (2-sided 95% CI) | Percent Mean (%) (2-sided 95% CI)
Study 1 (starting dose ZAVESCA 100 mg three times daily)
Baseline (Month 0) | 22 | 76.58
Month 12 Change from baseline |  | 8.28 (1.88, 14.69) | 16.0% (-0.8, 32.8)
Study 1 Extension Phase
Baseline (Month 0) | 13 | 72.35
Month 24 Change from baseline |  | 13.58 (7.72, 19.43) | 26.1% (14.7, 37.5)
Study 2 (ZAVESCA 50 mg three times daily)
Baseline (Month 0) | 17 | 116.47
Month 6 Change from baseline |  | 5.35 (-6.31, 17.02) | 2.0% (-6.9, 10.8)
Study 2 Extension Phase
Baseline (Month 0) | 13 | 122.15
Month 12 Change from baseline |  | 14.0 (-3.4, 31.4) | 14.7% (-1.4, 30.7)

Open-Label Active-Controlled Trial

Study 3 was an open-label, randomized, active-controlled study of 36 adult patients with type 1 Gaucher disease, who had been receiving enzyme replacement therapy with imiglucerase for a minimum of 2 years prior to study entry. Patients were randomized 1:1:1 to one of three treatment groups, as follows:

- ZAVESCA 100 mg three times daily alone
- imiglucerase (patient's usual dose) alone
- ZAVESCA 100 mg three times daily and imiglucerase (usual dose)

Patients were treated for 6 months, and 33 patients completed the study. Because ZAVESCA is only indicated as monotherapy, the results for the monotherapy arms are described below. At Month 6, the results showed a decrease in mean percent change in liver volume in the ZAVESCA treatment group compared to the imiglucerase alone group. There were no significant differences between the groups for mean absolute changes in liver and spleen volume and hemoglobin concentration. However, there was a significant difference between the ZAVESCA alone and imiglucerase alone groups in platelet counts at Month 6, with the ZAVESCA alone group having a mean absolute decrease in platelet count of 21.6×10^9/L and the imiglucerase alone group having a mean absolute increase in platelet count of 10.1×10^9/L (See Tables 7–10).

Extension period

Twenty-nine patients were enrolled in a 6-month extension to Study 3. In the extension phase, all 29 patients had withdrawn from imiglucerase and received open-label ZAVESCA 100 mg three times daily monotherapy. At Month 12, the results showed non-significant decreases in platelet counts from baseline in all the treatment groups (by original randomization). There was a significant decrease in platelet counts from Month 6 to Month 12 in the group originally randomized to treatment with imiglucerase, and a continued decrease in platelet counts in the group originally randomized to ZAVESCA alone. There were no significant changes in any treatment group for liver volume, spleen volume, or hemoglobin concentration (See Tables 7–10).

Liver volume results from Study 3 and extension are summarized in Table 7:

Table 7: Liver Volume Changes from Study 3 and Extension Phase
 | Imiglucerase alone | ZAVESCA alone
Study 3 | n=11 | n=10
Month 0 | 1.81 | 1.58
Month 6 Change (L) | 0.04 | -0.05
Month 6 % Change | 3.6% | -2.9%
Adjusted mean Difference from Imiglucerase (95% CI) |  | -4.5% (-13.2, 4.2)
Extension Phase [All patients received ZAVESCA 100 mg three times daily monotherapy from Month 6 to Month 12.] | n=10 | n=8
Month 0 | 1.94 | 1.60
Month 12 Change (L) | -0.05 | -0.01
Month 12 % Change | -0.7% | -0.8%

Spleen volume results from Study 3 and extension are summarized in Table 8:

Table 8: Spleen Volume Changes from Study 3 and Extension Phase
 | Imiglucerase alone | ZAVESCA alone
Study 3 | n=8 | n=7
Month 0 | 0.61 | 0.69
Month 6 Change (L) | -0.02 | -0.03
Month 6 % Change | -2.1% | -4.8%
Adjusted % Difference from Imiglucerase (95% CI) |  | -5.8% (-22.1, 10.5)
Extension Phase [All patients received ZAVESCA 100 mg three times daily monotherapy from Month 6 to Month 12.] | n=7 | n=6
Month 0 | 0.83 | 0.57
Month 12 Change (L) | 0.04 | -0.05
Month 12 % Change | 1.5% | -6.1%

Hemoglobin concentration results from Study 3 and extension are summarized in Table 9:

Table 9: Hemoglobin Concentration Changes from Study 3 and Extension Phase
 | Imiglucerase alone | ZAVESCA alone
Study 3 | n=12 | n=10
Month 0 | 13.18 | 12.44
Month 6 Change (g/dL) | -0.15 | -0.31
Month 6 % Change | -1.2% | -2.4%
Adjusted % Difference from Imiglucerase (95% CI) |  | -1.9% (-6.4, 2.6)
Extension Phase [All patients received ZAVESCA 100 mg three times daily monotherapy from Month 6 to Month 12 .] | n=10 | n=9
Month 0 | 13.39 | 12.46
Month 12 Change (g/dL) | -0.48 | -0.13
Month 12 % Change | -3.1% | -1.1%

Platelet count results from Study 3 and extension are summarized in Table 10:

Table 10: Platelet Count Changes from Study 3 and Extension Phase
 | Imiglucerase alone | ZAVESCA alone
Study 3 | n=12 | n=10
Month 0 | 165.75 | 170.55
Month 6 Change (10^9/L) | 15.29 | -21.60
Month 6 % Change | 10.1% | -9.6%
Adjusted % Difference from Imiglucerase (95% CI) |  | -17.1% (-32.9, -1.3)
Extension Phase [All patients received ZAVESCA 100 mg three times daily monotherapy from Month 6 to Month 12.] | n=10 | n=9
Month 0 | 170.05 | 184.83
Month 12 Change (10^9/L) | -3.75 | -27.39
Month 12 % Change | -3.2% | -10.4%

Patients with platelet counts above 150 × 10^9/L at baseline who were randomized to ZAVESCA treatment had significant decreases in platelet counts at Month 12.

16 HOW SUPPLIED/STORAGE AND HANDLING

ZAVESCA is supplied in hard gelatin capsules containing 100 mg of miglustat. ZAVESCA® 100 mg capsules are white opaque with "OGT 918" printed in black on the cap and "100" printed in black on the body.

ZAVESCA® 100 mg capsules are packed in blister cards. Six blister cards of 15 capsules are supplied in each carton.

NDC 66215-201-90: carton containing 90 capsules

NDC 66215-201-15: blister card containing 15 capsules

Storage

Store at 20°C to 25°C (68°F to 77°F). Excursions are permitted between 15°C to 30°C (59°F to 86°F), [See USP Controlled Room Temperature].

Keep out of reach of children.

17 PATIENT COUNSELING INFORMATION

Advise the patient to read the FDA-approved patient labeling (Patient Information).

Information for Patients

- Advise patients that the most common serious adverse reaction reported with ZAVESCA is peripheral neuropathy. Advise patients to promptly report any numbness, tingling, pain, or burning in the hands and feet [see Warnings and Precautions (5.1)] .
- Advise patients that other adverse reactions include tremor and reductions in platelet counts. Advise patients to promptly report the development of tremor or worsening in an existing tremor [see Warnings and Precautions (5.2, 5.4)].
- Advise patients that other serious adverse reactions include diarrhea and weight loss. Advise patients to adhere to dietary instructions [see Warnings and Precautions (5.3)] .
- Advise patients to take the next ZAVESCA capsule at the next scheduled time if a dose is missed.
- Inform patients of the potential risks and benefits of ZAVESCA and of alternative modes of therapy.

Pregnancy

Advise pregnant women and females of reproductive potential of the potential risk to a fetus, based on animal data. Advise patients who may become pregnant to inform their healthcare provider of a known or suspected pregnancy [see Use in Specific Populations (8.1)].

Lactation

Advise women not to breastfeed if they are taking ZAVESCA [see Use in Specific Populations (8.2)].

Manufactured for:

Actelion Pharmaceuticals US, Inc.,
a Janssen Pharmaceutical Company

Titusville, NJ 08560, USA

© 2003 – 2017 Actelion Pharmaceuticals US, Inc.

JN20220808

PATIENT INFORMATION
ZAVESCA® (zah-VEHS-kah)
(miglustat)
capsules

Read this Patient Information before you start taking ZAVESCA and each time you get a refill. There may be new information.

What is ZAVESCA?
ZAVESCA is a prescription medicine used alone to treat adults with mild to moderate type 1 Gaucher disease. ZAVESCA is used only in people who cannot be treated with enzyme replacement therapy.
It is not known if ZAVESCA is safe and effective in children under 18 years of age.

Before taking ZAVESCA, tell your healthcare provider about all of your medical conditions, including if you:

- have kidney problems
- are pregnant or plan to become pregnant. ZAVESCA may harm your unborn baby. Tell your healthcare provider right away if you become pregnant or think you may be pregnant during treatment with ZAVESCA.
- are breastfeeding or plan to breastfeed. It is not known if ZAVESCA can pass into your breast milk and may harm your baby . Do not breastfeed during treatment with ZAVESCA. Talk to your healthcare provider about the best way to feed your baby during treatment with ZAVESCA.

Tell your healthcare provider about all the medicines you take, including prescription and over-the-counter medicines, vitamins, and herbal supplements. ZAVESCA may affect how other medicines work.

How should I take ZAVESCA?

- Take ZAVESCA exactly as your healthcare provider tells you to.
- Take ZAVESCA at the same time each day.
- If you miss a dose of ZAVESCA, skip that dose. Take the next ZAVESCA capsule at the usual time.

What are the possible side effects of ZAVESCA?
ZAVESCA may cause serious side effects including:

- Numbness, tingling, pain, or burning in your hands or feet (peripheral neuropathy). Call your healthcare provider right away if you get numbness, tingling, pain, or burning in your hands or feet.
- Your healthcare provider may test your nerves (neurological exam) before you start ZAVESCA and during treatment with ZAVESCA.
- New or worsening hand tremors (shaky movements). Tremors are common with ZAVESCA and may begin within the first month of starting treatment. Sometimes the tremors may go away between 1 to 3 months with continued treatment. Your healthcare provider may lower your dose or stop ZAVESCA if you develop new or worsening hand tremors. Call your healthcare provider right away if you get new hand tremors during treatment with ZAVESCA or if the hand tremors you already have get worse.
- Diarrhea is common with ZAVESCA and sometimes can be serious. Your healthcare provider may prescribe another medicine (anti-diarrheal) to treat diarrhea if it is a problem for you and may recommend changes to your diet, such as avoiding foods high in carbohydrates. Talk with your healthcare provider about your diet if you have diarrhea.
- Weight loss is common with ZAVESCA and sometimes can be serious. You may lose weight when you start treatment with ZAVESCA.
- Low platelet count is common with ZAVESCA and can be serious. Your healthcare provider may do blood tests to monitor your blood platelet count during treatment with ZAVESCA.

The most common side effects of ZAVESCA include:

- weight loss
- stomach pain
- gas
- nausea and vomiting
- headache, including migraine
- back pain
- constipation
- dry mouth
- heaviness in arms and legs
- memory loss
- unsteady walking

- leg cramps
- dizziness
- weakness
- vision problems
- muscle cramps
- loss of appetite
- indigestion
- numbness, tingling, pain, or burning of your skin
- stomach bloating
- stomach pain not related to food
- menstrual changes

These are not all of the possible side effects of ZAVESCA.
Call your doctor for medical advice about side effects. You may report side effects to FDA at 1-800-FDA-1088.

How should I store ZAVESCA?

- Store ZAVESCA at room temperature between 68°F to 77°F (20°C to 25°C).

Keep ZAVESCA and all medicines out of the reach of children.

General information about the safe and effective use of ZAVESCA.
Medicines are sometimes prescribed for purposes other than those listed in a Patient Information leaflet. Do not use ZAVESCA for a condition for which it was not prescribed. Do not give ZAVESCA to other people, even if they have the same symptoms you have. It may harm them.
You can ask your healthcare provider or pharmacist for information about ZAVESCA that is written for health professionals.

What are the ingredients in ZAVESCA?
Active ingredient: miglustat
Inactive ingredients: sodium starch glycolate, povidone (K30), and magnesium stearate.
The capsule shell contains: gelatin and titanium dioxide; the edible printing ink contains black iron oxide and shellac.
Manufactured for: Actelion Pharmaceuticals US, Inc.,
a Janssen Pharmaceutical Company
Titusville, NJ 08560, USA
© 2003–2017 Actelion Pharmaceuticals US, Inc.
JN202200808
For more information, call Janssen at 1-800-526-7736 (1-800- JANSSEN) or go to www.ZAVESCA.com

This Patient Information has been approved by the U.S. Food and Drug Administration.

Revised: 01/2021

PRINCIPAL DISPLAY PANEL - 100 mg Capsule Blister Card Carton

NDC 66215-201-90

zavesca® 100 mg
(migLUstat) capsules

This package is not child resistant.

Contents:
90 Capsules (six blister cards of 15 capsules each)

Oral use

Rx only

janssen